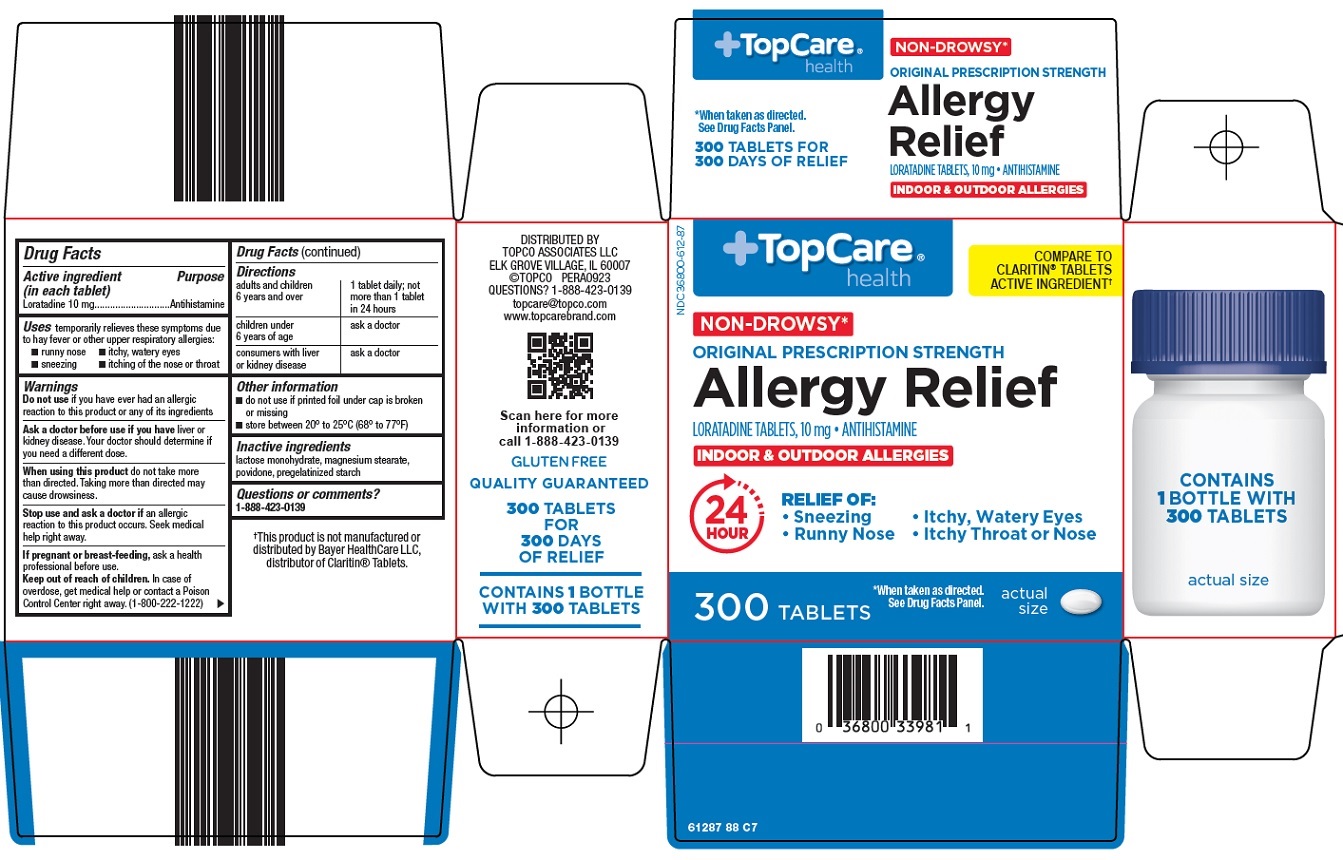 DRUG LABEL: TopCare Allergy Relief
NDC: 36800-612 | Form: TABLET
Manufacturer: Topco Associates LLC
Category: otc | Type: HUMAN OTC DRUG LABEL
Date: 20250328

ACTIVE INGREDIENTS: LORATADINE 10 mg/1 1
INACTIVE INGREDIENTS: LACTOSE MONOHYDRATE; MAGNESIUM STEARATE; POVIDONE, UNSPECIFIED

Topco Associates LLC. Allergy Relief Drug Facts

Active ingredient (in each tablet)

Loratadine 10 mg

Purpose

Antihistamine

Uses

temporarily relieves these symptoms due to hay fever or other upper respiratory allergies:

- runny nose
- itchy, watery eyes
- sneezing
- itching of the nose or throat

Warnings

Do not use

if you have ever had an allergic reaction to this product or any of its ingredients

Ask a doctor before use if you have

liver or kidney disease. Your doctor should determine if you need a different dose.

When using this product

do not take more than directed. Taking more than directed may cause drowsiness.

Stop use and ask a doctor if

an allergic reaction to this product occurs. Seek medical help right away.

If pregnant or breast-feeding,

ask a health professional before use.

Keep out of reach of children.

In case of overdose, get medical help or contact a Poison Control Center right away. (1-800-222-1222)

Directions

adults and children 6 years and over | 1 tablet daily; not more than 1 tablet in 24 hours
children under 6 years of age | ask a doctor
consumers with liver or kidney disease | ask a doctor

Other information

- do not use if blister unit is broken or torn
- store between 20° to 25°C (68° to 77°F)
- protect from excessive moisture

Inactive ingredients

lactose monohydrate, magnesium stearate, povidone, pregelatinized starch

Questions or comments?

1-888-423-0139

Principal Display Panel

TopCare® health

COMPARE TO CLARITIN® TABLETS ACTIVE INGREDIENT

NON-DROWSY*

ORIGINAL PRESCRIPTION STRENGTH

Allergy Relief

LORATADINE TABLETS, 10 mg ● ANTIHISTAMINE

INDOOR & OUTDOOR ALLERGIES

24 HOUR

RELIEF OF:

● Sneezing

● Runny Nose

● Itchy, Watery Eyes

● Itchy Throat or Nose

300 TABLETS

*When taken as directed. See Drug Facts Panel.

actual size